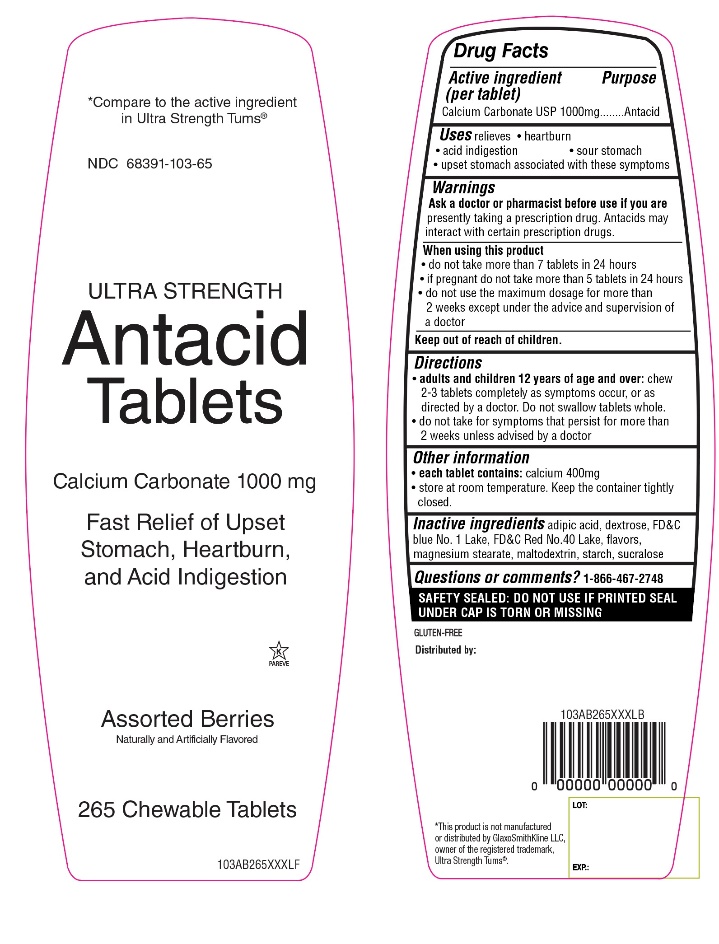 DRUG LABEL: BERKLEY JENSEN
NDC: 68391-033 | Form: TABLET, CHEWABLE
Manufacturer: BJWC
Category: otc | Type: HUMAN OTC DRUG LABEL
Date: 20250408

ACTIVE INGREDIENTS: CALCIUM CARBONATE 1000 mg/1 1
INACTIVE INGREDIENTS: ADIPIC ACID; DEXTROSE, UNSPECIFIED FORM; FD&C BLUE NO. 1; FD&C RED NO. 40; MAGNESIUM STEARATE; MALTODEXTRIN; STARCH, CORN; SUCRALOSE

Ultra Strength Antacid Tablets Calcium Carbonate Drug Facts

Active ingredient (per tablet)

Calcium Carbonate USP 1000mg

Purpose

Antacid

Uses

relieves

- heartburn
- acid indigestion
- sour stomach
- upset stomach associated with these symptoms

Ask a doctor or pharmacist before use if you are

presently taking a prescription drug. Antacids may interact with certain prescription drugs.

When using this product

- do not take more than 7 tablets in 24 hours
- if pregnant do not take more than 5 tablets in 24 hours
- do not use the maximum dosage for more than 2 weeks except under the advice and supervision of a doctor

Directions

- adults and children 12 years of age and over: chew 2-3 tablets, completely as symptoms occur, or as directed by a doctor. Do not swallow tablets whole.
- do not take for symptoms that persist for more than 2 weeks unless advised by a doctor

Other information

- each tablet contains: calcium 400mg
- store at room temperature. Keep the container tightly closed.

Inactive ingredients

adipic acid, dextrose, FD&C blue no. 1 Lake, FD&C red no. 40 Lake, flavors, magnesium stearate, maltodextrin, starch, sucralose.

Questions or comments?

1-866-467-2748

SAFETY SEALED

DO NOT USE IF PRINTED SEAL UNDER CAP IS TORN OR MISSING

Package/Label Principal Display Panel

*Compare to the active ingredient in Ultra Strength Tums®

NDC# 68391-033-65

ULTRA STRENGTH

Antacid Tablets

Calcium Carbonate 1000 mg

Fast Relief of Upset Stomach, Heartburn, and Acid Indigestion

Assorted Berries

Naturally and Artificially Flavored

GLUTEN FREE

265 CHEWABLE TABLETS

K PAREVE

*This product is not manufactured or distributed by GlaxoSmithKline LLC, owner of the registered trademark, Ultra Strength Tums®.